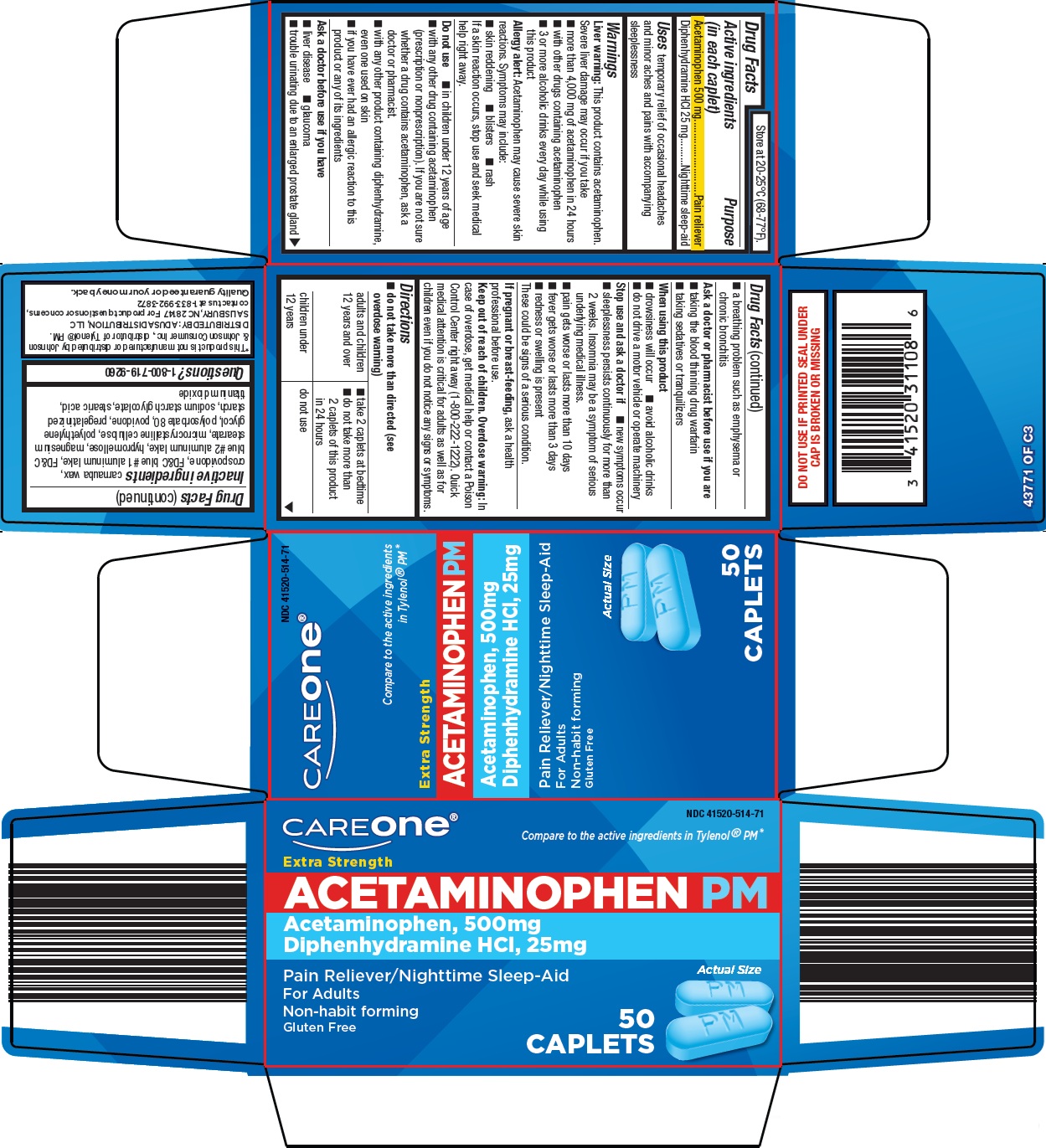 DRUG LABEL: CareOne Acetaminophen PM
NDC: 41520-514 | Form: TABLET, FILM COATED
Manufacturer: American Sales Company
Category: otc | Type: HUMAN OTC DRUG LABEL
Date: 20260205

ACTIVE INGREDIENTS: ACETAMINOPHEN 500 mg/1 1; DIPHENHYDRAMINE HYDROCHLORIDE 25 mg/1 1
INACTIVE INGREDIENTS: CARNAUBA WAX; CROSPOVIDONE, UNSPECIFIED; FD&C BLUE NO. 1 ALUMINUM LAKE; FD&C BLUE NO. 2 ALUMINUM LAKE; HYPROMELLOSE, UNSPECIFIED; MAGNESIUM STEARATE; MICROCRYSTALLINE CELLULOSE; POLYETHYLENE GLYCOL, UNSPECIFIED; POLYSORBATE 80; POVIDONE, UNSPECIFIED; SODIUM STARCH GLYCOLATE TYPE A; STEARIC ACID; TITANIUM DIOXIDE

American Sales Company Acetaminophen PM Drug Facts

Active ingredients (in each caplet)

Acetaminophen 500 mg

Diphenhydramine HCl 25 mg

Purpose

Pain reliever

Nighttime sleep-aid

Uses

temporary relief of occasional headaches and minor aches and pains with accompanying sleeplessness

Warnings

Liver warning: This product contains acetaminophen. Severe liver damage may occur if you take

- more than 4,000 mg of acetaminophen in 24 hours
- with other drugs containing acetaminophen
- 3 or more alcoholic drinks every day while using this product

Allergy alert: Acetaminophen may cause severe skin reactions. Symptoms may include:

- skin reddening
- blisters
- rash

If a skin reaction occurs, stop use and seek medical help right away.

Do not use

- in children under 12 years of age
- with any other drug containing acetaminophen (prescription or nonprescription). If you are not sure whether a drug contains acetaminophen, ask a doctor or pharmacist.
- with any other product containing diphenhydramine, even one used on skin
- if you have ever had an allergic reaction to this product or any of its ingredients

Ask a doctor before use if you have

- liver disease
- glaucoma
- trouble urinating due to an enlarged prostate gland
- a breathing problem such as emphysema or chronic bronchitis

Ask a doctor or pharmacist before use if you are

- taking the blood thinning drug warfarin
- taking sedatives or tranquilizers

When using this product

- drowsiness will occur
- avoid alcoholic drinks
- do not drive a motor vehicle or operate machinery

Stop use and ask a doctor if

- new symptoms occur
- sleeplessness persists continuously for more than 2 weeks. Insomnia may be a symptom of serious underlying medical illness.
- pain gets worse or lasts more than 10 days
- fever gets worse or lasts more than 3 days
- redness or swelling is present

These could be signs of a serious condition.

If pregnant or breast-feeding,

ask a health professional before use.

Keep out of reach of children.

Overdose warning: In case of overdose, get medical help or contact a Poison Control Center right away (1-800-222-1222). Quick medical attention is critical for adults as well as for children even if you do not notice any signs or symptoms.

Directions

- do not take more than directed (see overdose warning)

adults and children 12 years and over | - take 2 caplets at bedtime - do not take more than 2 caplets of this product in 24 hours
children under 12 years | do not use

Inactive ingredients

carnauba wax, crospovidone, FD&C blue #1 aluminum lake, FD&C blue #2 aluminum lake, hypromellose, magnesium stearate, microcrystalline cellulose, polyethylene glycol, polysorbate 80, povidone, pregelatinized starch, sodium starch glycolate, stearic acid, titanium dioxide

Principal Display Panel

CAREone®

Compare to the active ingredients in Tylenol® PM

Extra Strength

ACETAMINOPHEN PM

Acetaminophen, 500mg

Diphenhydramine HCl, 25mg

Actual Size

Pain Reliever/Nighttime Sleep-Aid

For Adults

Non-habit forming

Gluten Free

50 CAPLETS